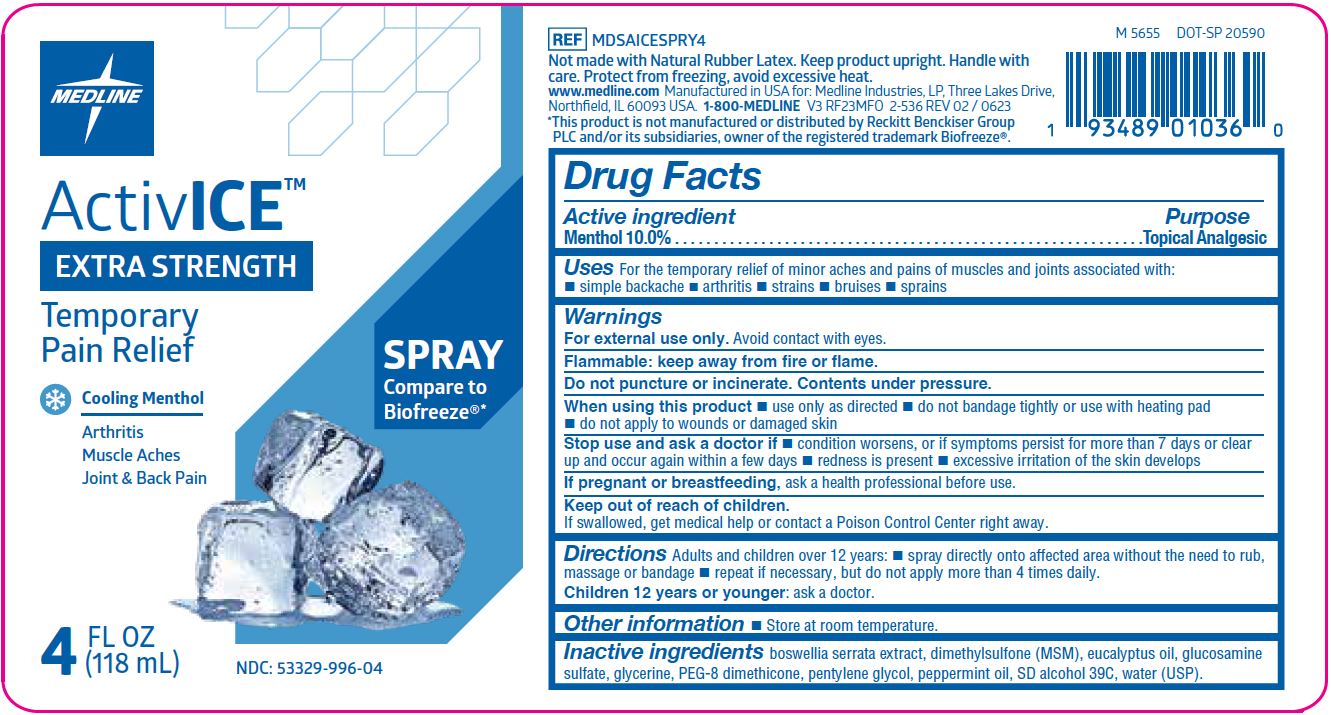 DRUG LABEL: ActivICE
NDC: 53329-996 | Form: SPRAY
Manufacturer: Medline Industries, LP
Category: otc | Type: HUMAN OTC DRUG LABEL
Date: 20241212

ACTIVE INGREDIENTS: MENTHOL 100 mg/1 mL
INACTIVE INGREDIENTS: INDIAN FRANKINCENSE; EUCALYPTUS OIL; GLUCOSAMINE SULFATE; ALCOHOL; PEG-8 DIMETHICONE; GLYCERIN; PENTYLENE GLYCOL; WATER; PEPPERMINT OIL; DIMETHYL SULFONE

996 ActivICE™ Extra Strength Temporary Pain Relief, Spray

Active ingredient

Menthol 10.0%

Purpose

Topical analgesic

Uses

For the temporary relief of minor aches and pains of muscles and joints associated with:

- simple backache
- arthritis
- strains
- bruises
- sprains

Warnings

For external use only. Avoid contact with eyes

Flammable: keep away from fire or flame

Do not puncture or incinerate. Contents under pressure.

When using this product

- use only as directed
- do not bandage tightly or use with heating pad
- do not apply to wounds or damaged skin

Stop use and ask doctor if

- condition worsens, or if symptoms persist for more than 7 days or clear up and occur again within a few days
- redness is present
- excessive irritation of the skin develops

If pregnant or breastfeeding,

ask a health professional before use.

Keep our of reach of children.

If swallowed, get medical help or contact a Poison Control Center right away.

Directions

Adults and children over 12 years:

- spray directly onto affected area without the need to rub, massage or bandage
- repeat if necessary, but do not apply more than 4 times daily

Children 12 years or younger:

- ask a doctor

Other information

- store at room temperature

Inactive ingredients

boswellia serrata extract, dimethylsulfone (MSM), eucalyptus oil, glucosamine sulfate, glycerine, SD alcohol 39C, PEG-8 dimethicone, pentylene glycol, peppermint oil, water (USP)

Manufacturing information

Manufactured for:
Medline Industries, LP
Three Lakes Drive, Northfield, IL 60093 USA
Made in USA with
www.medline.com
1-800-MEDLINE (633-5463)
REF: MDSAICESPRY4
V3 RF23MFO

*This product is not manufactured or distributed by Performance Health and/or its subsidiaries, owner of the registered trademark Biofreeze®.